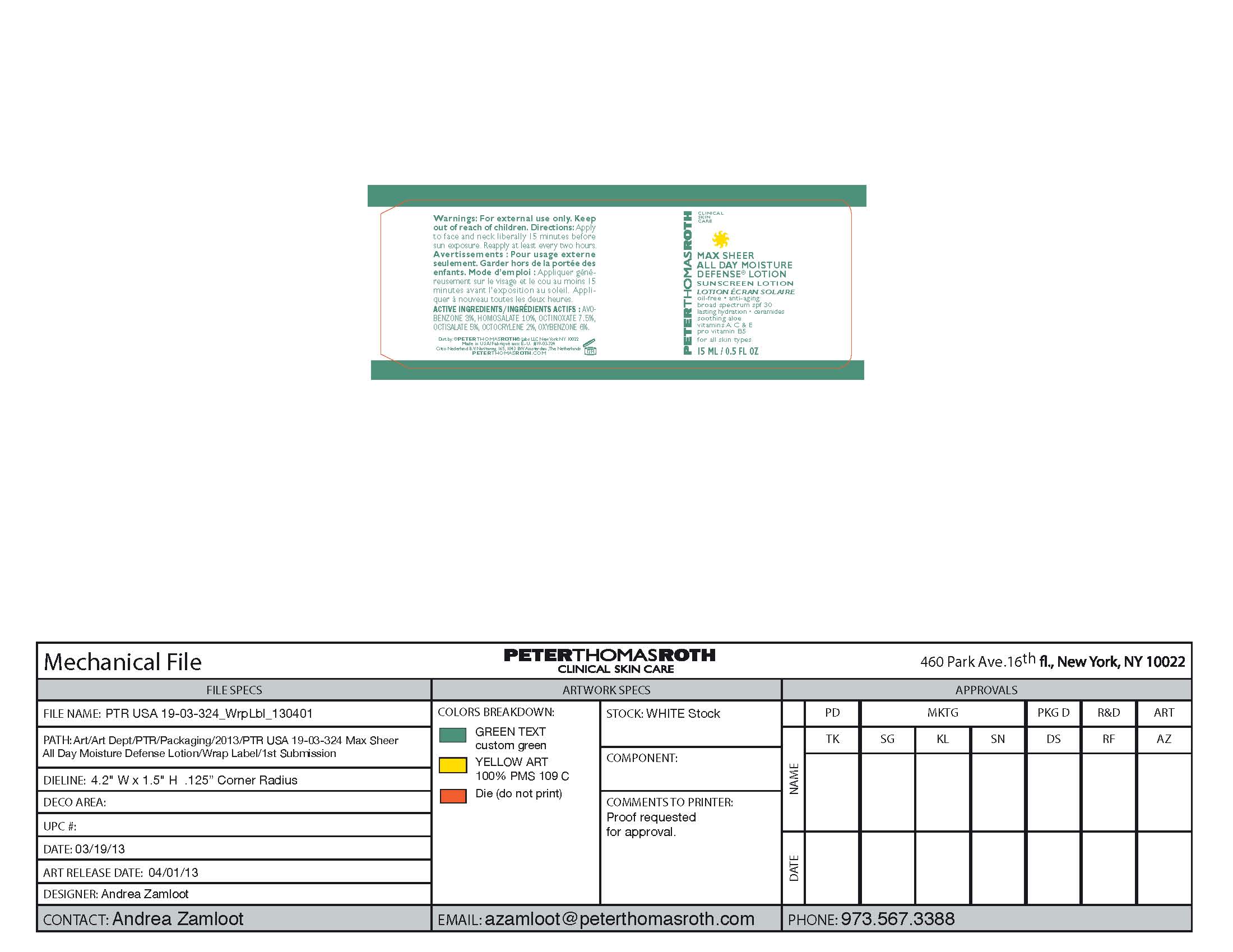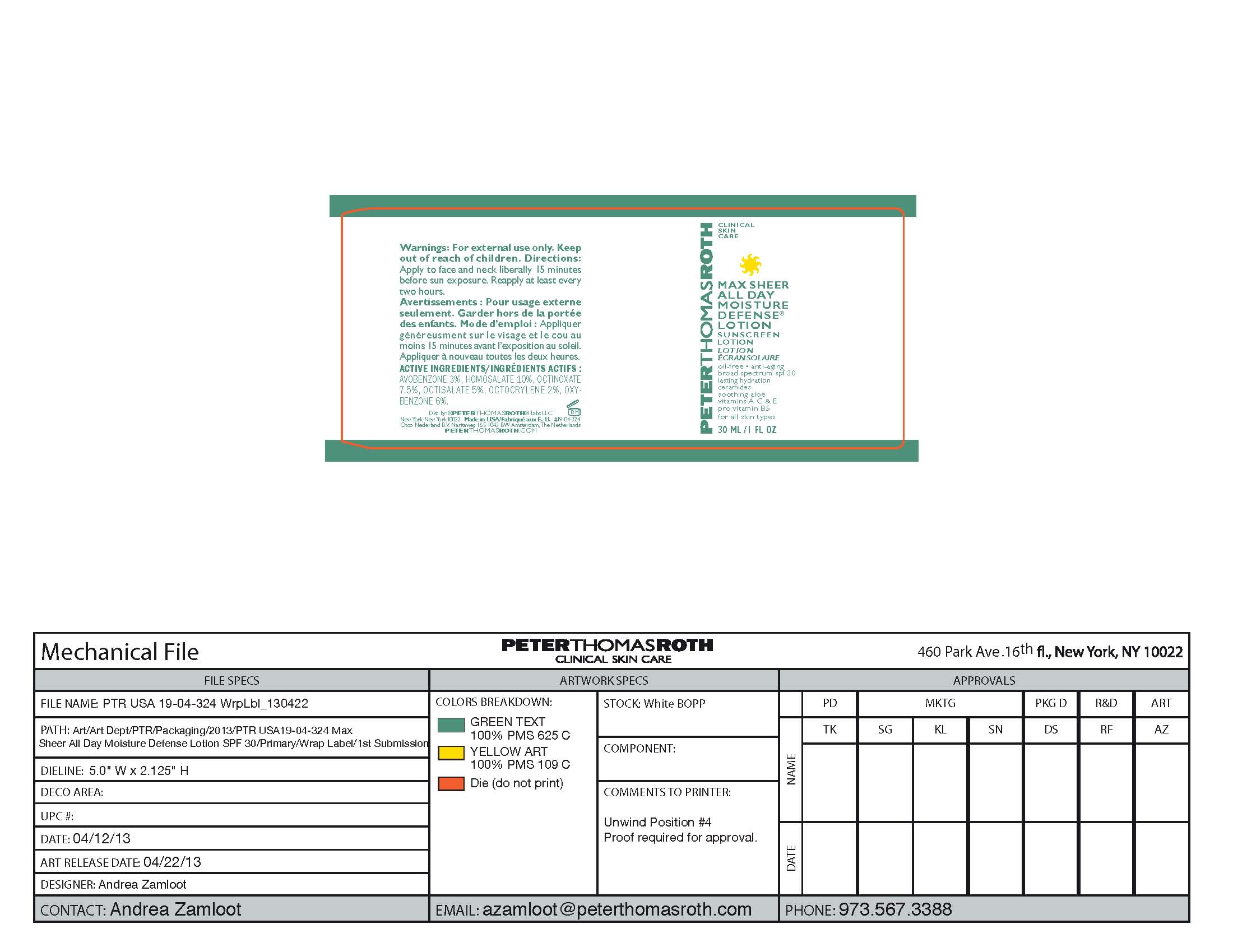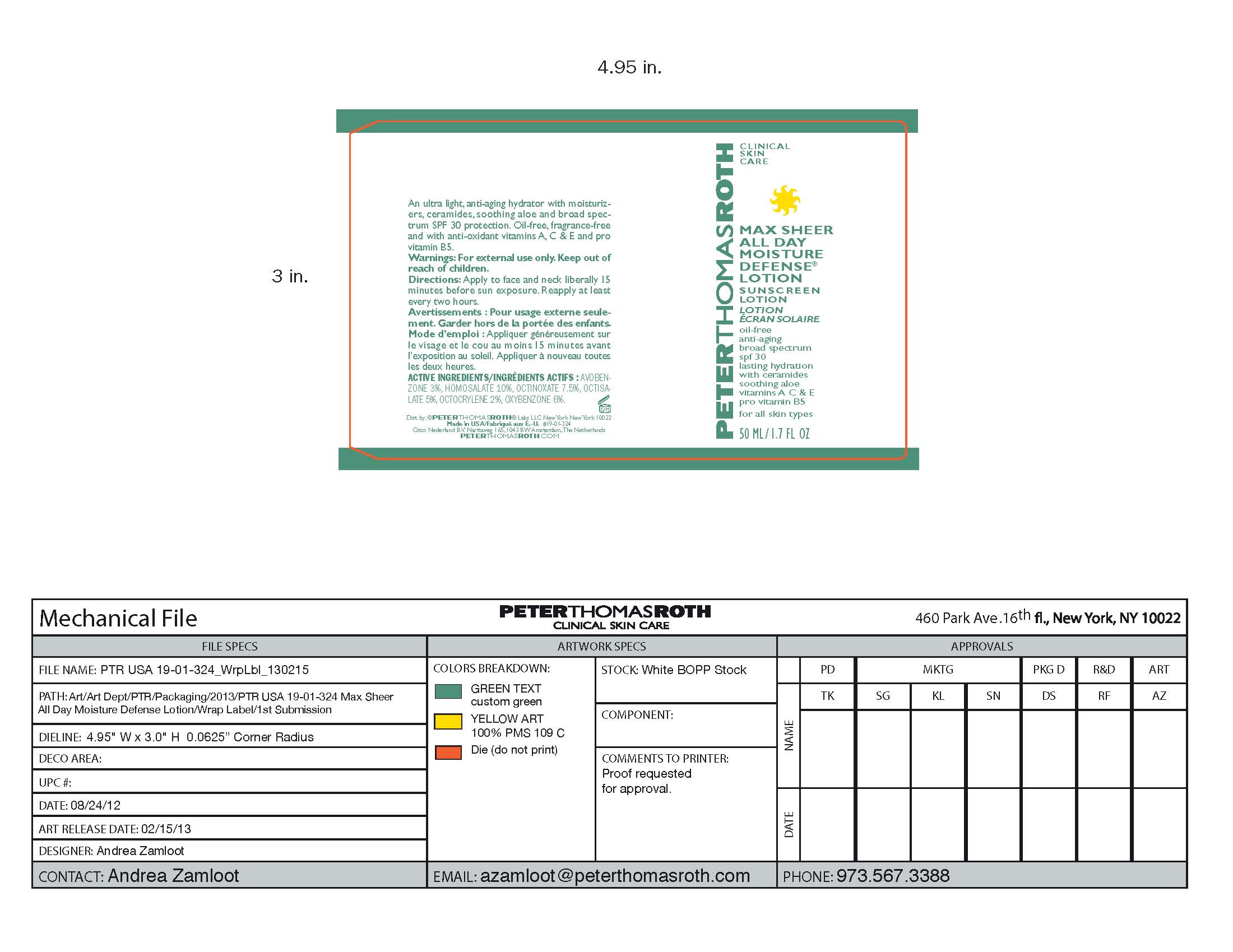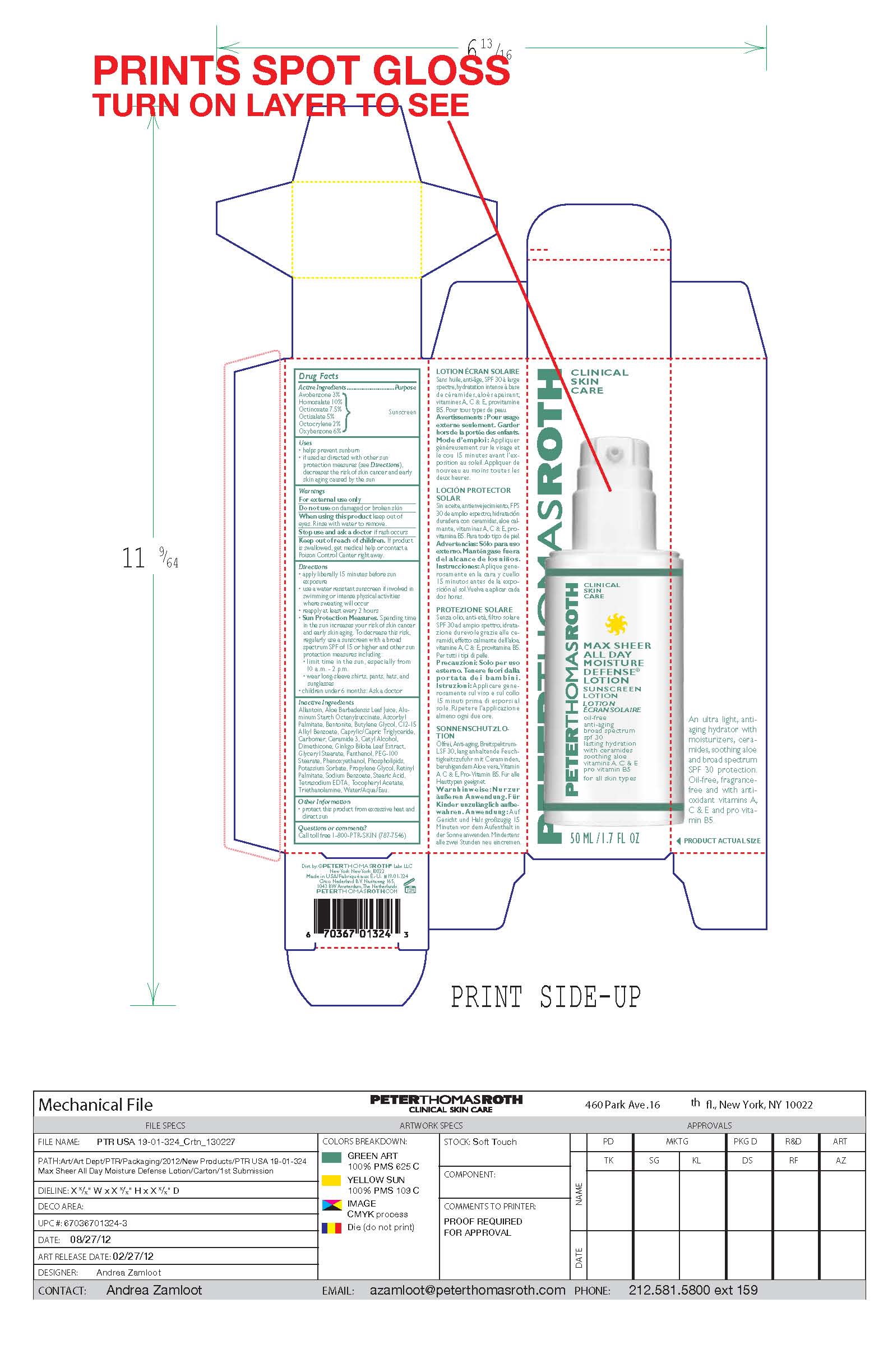 DRUG LABEL: Max Sheer All Day Moisture Defense
NDC: 54031-324 | Form: LOTION
Manufacturer: Peter Thomas Roth Labs LLC
Category: otc | Type: HUMAN OTC DRUG LABEL
Date: 20160628

ACTIVE INGREDIENTS: HOMOSALATE .001 g/1 mL; OCTINOXATE .0008 g/1 mL; OXYBENZONE .0006 g/1 mL; OCTISALATE .0005 g/1 mL; AVOBENZONE .0003 g/1 mL; OCTOCRYLENE .0002 g/1 mL
INACTIVE INGREDIENTS: WATER 0.0048 g/1 mL; Propylene Glycol 0.0004 g/1 mL; GLYCERYL 1-STEARATE 0.0003 g/1 mL; PEG-100 Stearate 0.00025 g/1 mL; ALKYL (C12-15) BENZOATE 0.0003 g/1 mL; MEDIUM-CHAIN TRIGLYCERIDES 0.0002 g/1 mL; Palmitic Acid 0.0002 g/1 mL; Phenoxyethanol 0.0001 g/1 mL; Stearic Acid 0.0001 g/1 mL; TROLAMINE 0.0001 g/1 mL; Bentonite 0.000025 g/1 mL; CARBOMER 940 0.000025 g/1 mL; Dimethicone 0.000025 g/1 mL; Allantoin 0.00002 g/1 mL; PEG-8 Dimethicone 0.000014 g/1 mL; ALOE VERA LEAF 0.00001 g/1 mL; Cetyl Alcohol 0.00001 g/1 mL; Panthenol 0.00001 g/1 mL; Aluminum Starch Octenylsuccinate 0.0000087 g/1 mL; EDETATE SODIUM 0.0000084 g/1 mL; Myristic Acid 0.000006 g/1 mL; Potassium Sorbate 0.0000025 g/1 mL; Sodium Benzoate 0.0000025 g/1 mL; Arachidic Acid 0.000002 g/1 mL; Lauric Acid 0.000002 g/1 mL; Ascorbic Acid 0.000001 g/1 mL; Octyldodecanol 0.000001 g/1 mL; VITAMIN A PALMITATE 0.000001 g/1 mL; SILICON DIOXIDE 0.000001 g/1 mL; Sodium Propoxyhydroxypropyl Thiosulfate Silica 0.000001 g/1 mL; .ALPHA.-TOCOPHEROL ACETATE 0.000001 g/1 mL; Ceramide NP 0.00000099 g/1 mL; Butylene Glycol 0.000000395 g/1 mL; GINKGO 0.0000002 g/1 mL; Butyl Acetate 0.000000001 g/1 mL

Peter Thomas Roth Max Sheer All Day Moisture Defense Lotion Sunscreen SPF 30

Drug Facts

Active Ingredients

Avobenzone 3%
Homosalate 10%
Octinoxate 7.5%
Octisalate 5%
Octocrylene 2%
Oxybenzone 6%

Purpose

Sunscreen

Uses

- helps prevent sunburn
- if used as directed with other sun protection measures (see Directions), decreases the risk of skin cancer and early skin aging caused by the sun.

Warnings

For external use only

- Do not use on damaged or broken skin

When using this product keep out of eyes. Rinse with water to remove.

- Stop use and ask a doctor if rash occurs

- Keep out of reach of children.
- If product is swallowed, get medical help or contact a Poison Control Center right away.

Directions

- apply liberally 15 minutes before sun exposure
- use a water resistant sunscreen if involved in swimming or intense physical activities where sweating will occur
- reapply at least every 2 hours
- Sun Protection Measures. Spending time in the sun increases your risk of skin cancer and early skin aging. To decrease this risk, regularly use a sunscreen with a broad spectrum SPF of 15 or higher and other sun protection measures including:
- limit time in the sun, especially from 10 a.m. - 2 p.m.
- wear long-sleeve shirts, pants, hats, and sunglasses
- children under 6 months: Ask a doctor

Inactive Ingredients

Allantoin, Aloe Barbadensis Leaf Juice, Aluminum Starch Octenylsuccinate, Ascorbyl Palmitate, Bentonite, Butylene Glycol, C12-15 Alkyl Benzoate, Caprylic/Capric Triglyceride, Carbomer, Ceramide 3, Cetyl Alcohol, Dimethicone, Ginkgo Biloba Leaf Extract, Glyceryl Stearate, Panthenol, PEG-100 Stearate, Phenoxyethanol, Phospholipids, Potassium Sorbate, Propylene Glycol, Retinyl Palmitate, Sodium Benzoate, Stearic Acid, Tetrasodium EDTA, Tocopheryl Acetate, Triethanolamine, Water/Aqua/Eau.

Other Information

protect this product from excessive heat and direct sun

Questions or comments?

Call toll free 1-800-PTR-SKIN (787-7546)